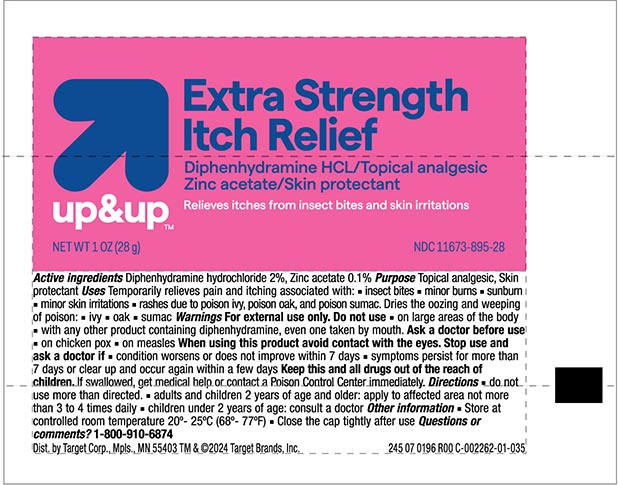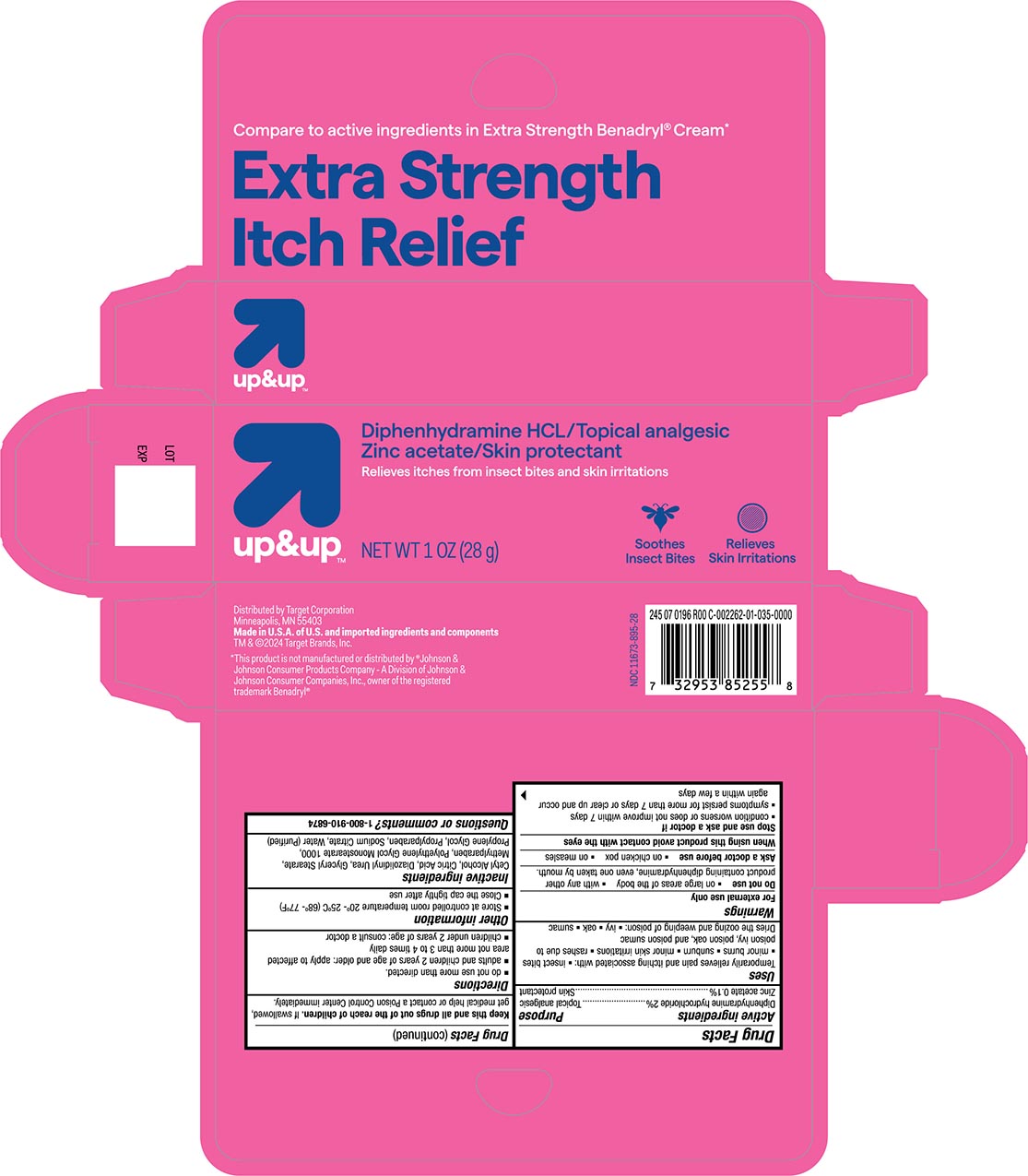 DRUG LABEL: Anti-itch
NDC: 11673-895 | Form: CREAM
Manufacturer: Target Corporation
Category: otc | Type: HUMAN OTC DRUG LABEL
Date: 20240117

ACTIVE INGREDIENTS: DIPHENHYDRAMINE HYDROCHLORIDE 20 mg/1 g; ZINC ACETATE 1 mg/1 g
INACTIVE INGREDIENTS: CETYL ALCOHOL; ANHYDROUS CITRIC ACID; DIAZOLIDINYL UREA; GLYCERYL STEARATE SE; METHYLPARABEN; POLYETHYLENE GLYCOL 10000; PROPYLENE GLYCOL; PROPYLPARABEN; SODIUM CITRATE; WATER

Target Up &Up Anti-itch Cream

Active Ingredients

Diphenhydramine HCL 2%

Zinc Acetate 0.1%

Purpose

Topical analgesic

Skin protectant

Uses

For temporary relief from pain and itching associated with :

- insect bites
- minor burns
- sunburn
- minor skin irritations
- rashes due to poison ivy, poison oak, and poison sumac

Dries the oozing and weeping of poison

- ivy
- oak
- sumac

Warnings For external use only

Do not use

- on large areas of the body
- with any other product containing diphenhydramine , even one taken by the mouth.

Ask a Doctor before use

- on chicken pox
- on measles

When using this product avoid contact with eyes.

Stop use and ask a doctor if

- conditions worsen or does not improve within 7 days
- symptoms persist for more than 7 days or clear up and occur agian within a few days

KEEP OUT OF REACH OF CHILDREN

Keep this and all drugs out of the reach of children. If swallowed get medical help or contact a Poison Control Center immediately.

Directions

- do not use more than directed
- adults and children 2 years of age and older; apply to affected areas not more than 3 to 4 times daily
- children under 2 years of age , consult a doctor

Other information

Store at controlled room temperature 20°-25°C (68° - 77°F)
Close the cap tightly after use

Inactive ingredients

Cetyl Alcohol, Citric Acid, Diazolldinyl Urea, Glyceral Stearate, Methylparaben, Polyethylene Glycol Monsterate 1000, Sodium Citrate, Water

(Purified)

Principal Display Panel

Target Up&Up NDC 11673-865-28

Extra Strength Itch Relief

Diphenhydramine HCL 2% / Zinc Aceate 0.1%

Anti-itch cream

NET WT 1 OZ (28g)